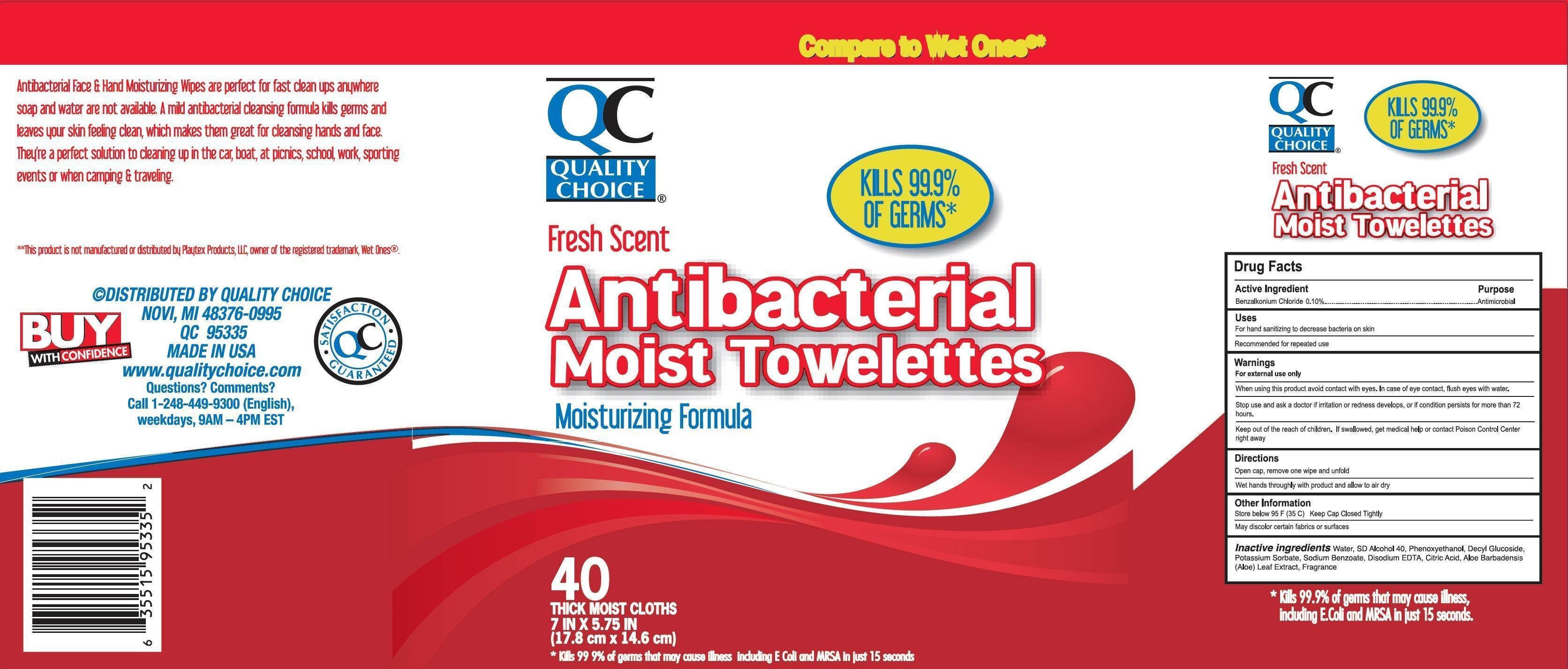 DRUG LABEL: QUALITY CHOICE Antibacterial Moist Towelettes
NDC: 63868-100 | Form: CLOTH
Manufacturer: Chain Drug Marketing Association
Category: otc | Type: HUMAN OTC DRUG LABEL
Date: 20130103

ACTIVE INGREDIENTS: BENZALKONIUM CHLORIDE 0.10 g/1 1
INACTIVE INGREDIENTS: WATER; PHENOXYETHANOL; DECYL GLUCOSIDE; POTASSIUM SORBATE; SODIUM BENZOATE; EDETATE DISODIUM; CITRIC ACID MONOHYDRATE; ALOE VERA LEAF

Drug Facts

Active Ingredient

Benzalkonium Chloride 0.10%

Purpose

Antimicrobial

Uses

For hand sanitizing to decrease bacteria on skin.
Recommended for repeated use.

Warnings

For external use only

When using this product

avoid contact with eyes. In case of eye contact, flush eyes with water.

Stop use and ask a doctor

if irritation or redness develpos, or if condition persists for more than 72 hours.

Keep out of reach of children.

If swallowed , get medical help or contact Poison Control Center right away.

Directions

Open cap, remove one wipe and unfold.
Wet hands throughly with product and allow to air dry.

Other Information

Store below 95 F(35C) Keep Cap-Closed Tightly
May discolor certain fabrics or surfaces.

Inactive ingredients

Water, SD Alcohol 40, Phenoxyethanol, Decyl Glucoside, Potassium Sorbate, Sodium Benzoate, Disodium EDTA, Citric Acid, Aloe Barbadensis (Aloe) Leaf Extract, Fragrance

Principal Display Panel

Compare to Wet Ones**
QC
QUALITY
CHOICE
KILLS 99.9%
OF GERMS*
Fresh Scent
Antibacterial
Moist Towelettes
Moisturizing Formula
40
THICK MOIST CLOTHS
7 IN X 5.75 IN
(17.8 cm x 14.6 cm)
*Kills 99.9 %of germs that may cause illness including E Coli and MRSA in just 15 seconds